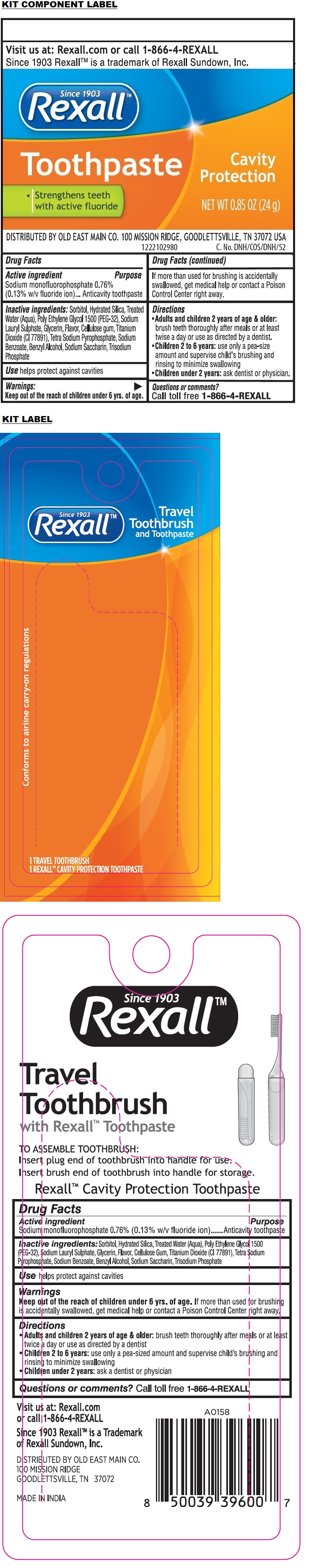 DRUG LABEL: Rexall Travel Toothbrush and Tooth-paste
NDC: 55910-087 | Form: KIT | Route: DENTAL
Manufacturer: Old East Main CO.
Category: otc | Type: HUMAN OTC DRUG LABEL
Date: 20241014

ACTIVE INGREDIENTS: SODIUM MONOFLUOROPHOSPHATE 1.3 mg/1 g
INACTIVE INGREDIENTS: SORBITOL; HYDRATED SILICA; WATER; POLYETHYLENE GLYCOL 1600; SODIUM LAURYL SULFATE; GLYCERIN; CARBOXYMETHYLCELLULOSE SODIUM, UNSPECIFIED; TITANIUM DIOXIDE; SODIUM PYROPHOSPHATE; SODIUM BENZOATE; BENZYL ALCOHOL; SACCHARIN SODIUM; SODIUM PHOSPHATE, TRIBASIC, ANHYDROUS

Rexall™ Travel Toothbrush and Toothpaste

Active ingredient

Sodium monofluorophosphate 0.76%
(0.13% w/v fluoride ion)

Purpose

Anticavity toothpaste

Inactive ingredients:

Sorbitol, Hydrated Silica, Treated Water (Aqua), Poly Ethylene Glycol 1500 (PEG-32), Sodium Lauryl Sulphate, Glycerin, Flavor, Cellulose Gum, Titanium Dioxide (CI 77891), Tetra Sodium Pyrophosphate, Sodium Benzoate, Benzyl Alcohol, Sodium Saccharin, Trisodium Phosphate

Use

helps protect against cavities

Warnings:

KEEP OUT OF REACH OF CHILDREN

Keep out of the reach of children under 6 yrs. of age.

If more than used for brushing is accidentally swallowed, get medical help or contact a Poison Control Center right away.

Directions

• Adults and children 2 years of age & older: brush teeth thoroughly after meals or at least twice a day or use as directed by a dentist.
• Children 2 to 6 years: use only a pea-sized amount and supervise child's brushing and rinsing to minimize swallowing
• Children under 2 years: ask a dentist or physician.

Questions or comments?

Call toll free 1-866-4-REXALL

Conforms to airline carry-on regulations

TO ASSEMBLE TOOTHBRUSH:
Insert plug end of toothbrush into handle for use.
Insert brush end of toothbrush into handle for storage.

Visit us at : Rexall.com

Since 1903 Rexall™ is a Trademark of Rexall Sundown, Inc.

DISTRIBUTED BY OLD EAST MAIN CO.
100 MISSION RIDGE
GOODLETTSVILLE, TN 37072

MADE IN INDIA